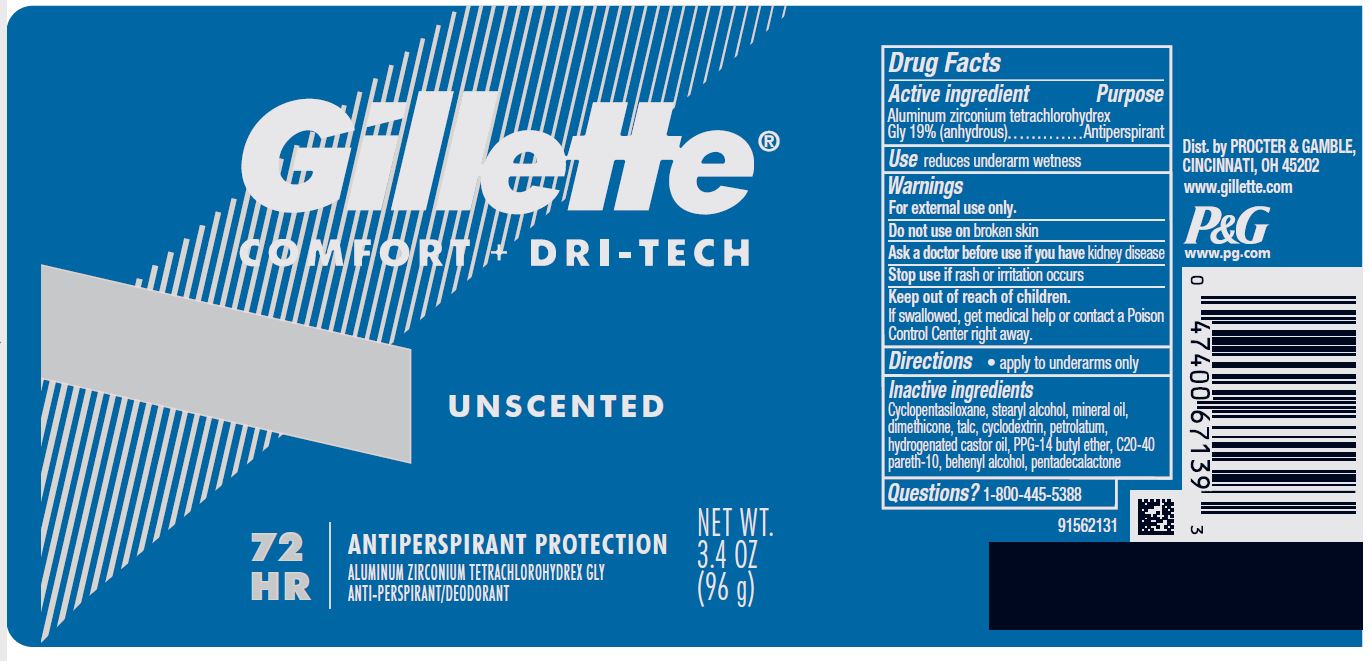 DRUG LABEL: Gillette Comfort plus Dri-Tech Unscented
NDC: 69423-650 | Form: STICK
Manufacturer: The Procter & Gamble Manufacturing Company
Category: otc | Type: HUMAN OTC DRUG LABEL
Date: 20221202

ACTIVE INGREDIENTS: ALUMINUM ZIRCONIUM TETRACHLOROHYDREX GLY 19 g/100 g
INACTIVE INGREDIENTS: PENTADECALACTONE; C20-40 PARETH-10; DIMETHICONE; CYCLOMETHICONE 5; STEARYL ALCOHOL; MINERAL OIL; TALC; HYDROGENATED CASTOR OIL; PPG-14 BUTYL ETHER; DOCOSANOL; PETROLATUM; BETADEX

Gillette Comfort + Dri-Tech Unscented

Drug Facts

Active ingredient

Aluminum zirconium tetrachlorohydrex Gly 19% (anhydrous)

Purpose

Antiperspirant

Use

reduces underarm wetness

Warnings

For external use only.

Do not use on broken skin

Ask a doctor before use if you have kidney disease

Stop use if rash or irritation occurs

Keep out of reach of children.
If swallowed, get medical help or contact a Poison Control Center right away.

Directions

- apply to underarms only

Inactive ingredients

Cyclopentasiloxane, stearyl alcohol, mineral oil, dimethicone, talc, cyclodextrin, petrolatum, hydrogenated castor oil, PPG-14 butyl ether, C20-40 pareth-10, behenyl alcohol, pentadecalactone

Questions?

1-800-445-5388

Dist. by PROCTER & GAMBLE,
CINCINNATI, OH 45202.

PRINCIPAL DISPLAY PANEL - 96 g Cylinder Label

Gillette®

Comfort + Dri-Tech

Unscented

72 HR ANTIPERSPIRANT PROTECTION

ALUMINUM ZIRCONIUM TETRACHLOROHYDREX GLY

ANTI-PERSPIRANT/DEODORANT

NET WT. 3.4 OZ (96 g)